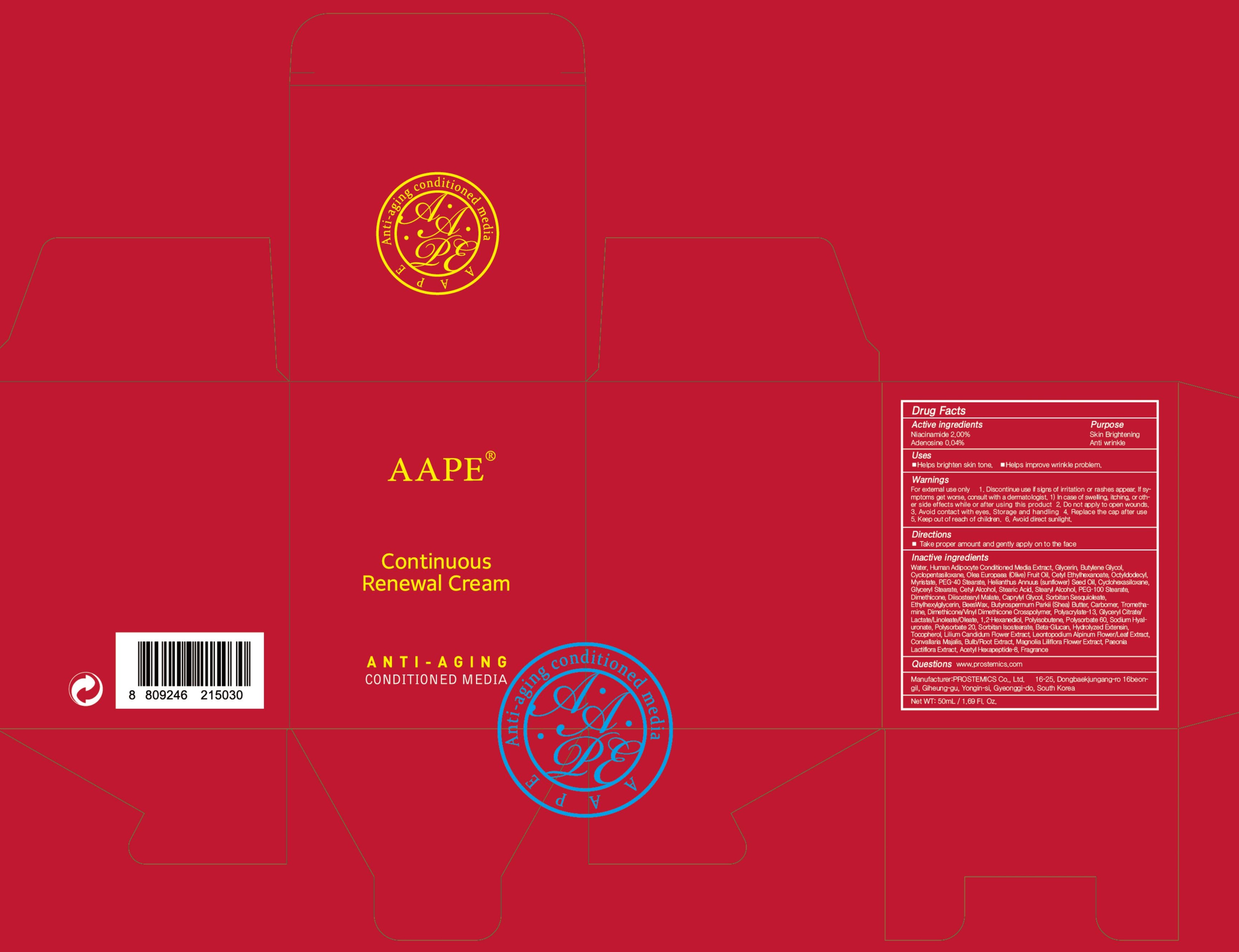 DRUG LABEL: AAPE Continuous Renewal
NDC: 62041-220 | Form: CREAM
Manufacturer: PROSTEMICS Co., Ltd.
Category: otc | Type: HUMAN OTC DRUG LABEL
Date: 20190826

ACTIVE INGREDIENTS: Niacinamide 1.00 g/50 mL; Adenosine 0.02 g/50 mL
INACTIVE INGREDIENTS: Water; Glycerin

ACTIVE INGREDIENT

Active ingredients: Niacinamide 2.00%, Adenosine 0.04%

INACTIVE INGREDIENT

Inactive ingredients:
Water, Human Adipocyte Conditioned Media Extract
Glycerin, Butylene Glycol, Cyclopentasiloxane, Olea Europaea (Olive), Fruit Oil, Cetyl Ethylhexanoate, Octyldodecyl, Myristate, PEG-40 Stearate, Helianthus Annuus (sunflower) Seed Oil, Cyclohexasiloxane, Glyceryl Stearate, Cetyl Alcohol, Stearic Acid, Stearyl Alcohol, PEG-100 Stearate, Dimethicone, Diisostearyl Malate, Caprylyl Glycol, Sorbitan Sesq ioleate, Ethylhexylglycerin, BeesWax, Butyrospermum Parkii (Shea) Butter, Carbomer, Tromethamine, Dimethicone/Vinyl Dimethicone Crosspolymer, Polyacrylate-13, Glyceryl Citrate/Lactate/Linoleate/Oleate, 1,2-Hexanediol, Polyisobutene, Polysorbate 60, Sodium Hyaluronate, Polysorbate 20, Sorbitan Isostearate, Beta-Glucan, Hydrolyzed, Extensin, Tocopherol, Lilium Candidum Flower Extract, Leontopodium Alpinum Flower/Leaf Extract, Convallaria Majalis, Bulb/Root Extract, Magnolia Liliflora Flower Extract, Paeonia Lactiflora Extract, Acetyl Hexapeptide-8, Fragrance

PURPOSE

Purpose: Skin Brightening, Anti wrinkle

WARNINGS

For external use only
1. Discontinue use if signs of irritation or rashes appear. If symptoms get worse, consult with a dermatologist. 1) In case of swelling, itching, or other side effects while or after using this product
2. Do not apply to open wounds.
3. Avoid contact with eyes.
Storage and handling
4. Replace the cap after use
5. Keep out of reach of children.
6. Avoid direct sunlight.

KEEP OUT OF REACH OF CHILDREN

Uses

Helps brighten skin tone.

Helps improve wrinkle problem.

Directions

Take proper amount and gently apply on to the face.